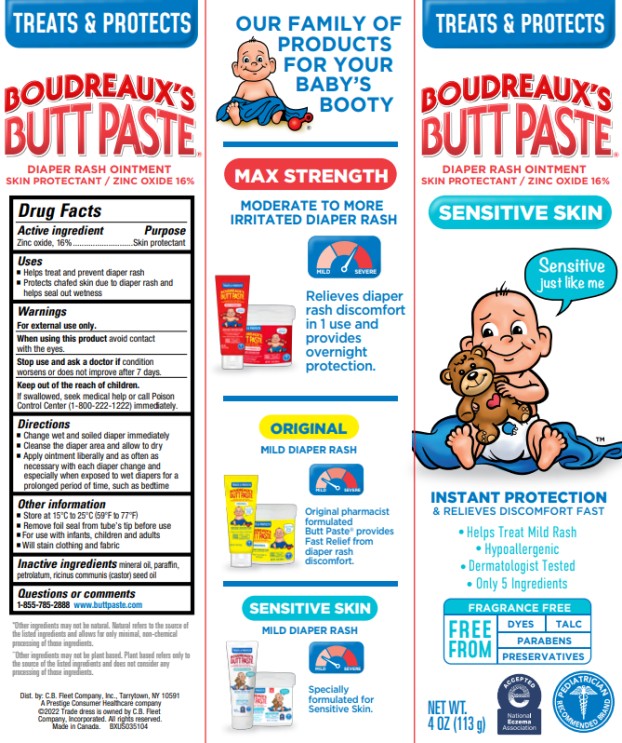 DRUG LABEL: Boudreauxs
NDC: 0132-0324 | Form: OINTMENT
Manufacturer: C.B. Fleet Company, Inc.
Category: otc | Type: HUMAN OTC DRUG LABEL
Date: 20250116

ACTIVE INGREDIENTS: ZINC OXIDE 16 g/113 g
INACTIVE INGREDIENTS: MINERAL OIL; PARAFFIN; PETROLATUM; CASTOR OIL

Boudreauxs Sensitive_0132-0324-04

Drug Facts

Active ingredient

Zinc oxide, 16%

Purpose

Skin protectant

Uses

- Helps treat and prevent diaper rash
- Protects chafed skin due to diaper rash and helps seal out wetness

Warnings

For external use only

When using this product

avoid contact with the eyes

Stop use and ask a doctor if

condition worsens or does not improve after 7 days

Keep out of reach of children

If swallowed, seek medical help or call poison control center (1-800-222-1222)

Directions

- Change wet and soiled diaper immediately
- Cleanse the diaper area and allow to dry
- Apply ointment liberally and as often as necessary with each diaper change and especially when exposed to wet diapers for a prolonged period of time, such as bedtime

Other information

- Store at 15-25⁰ C (59-77⁰ F)
- Remove foil seal from tube’s tip before use
- For use with infants, children and adults
- Will stain clothing and fabric

Inactive ingredients

mineral oil, paraffin, petrolatum, ricinus communis (castor) seed oil

Dist by C. B. Fleet Company, Inc.
Tarrytown, NY 10591
A Prestige Consumer Healthcare company
© 2019 Trade dress is owned by C.B. Fleet company Inc.
All rights reserved. Made in USA

PRINCIPAL DISPLAY PANEL

TREATS & PROTECTS

Boudreaux’s® Butt Paste

Diaper rash ointment

Skin protectant /16% zinc oxide

Sensitive Skin

NET WT. 4 OZ (113 g)